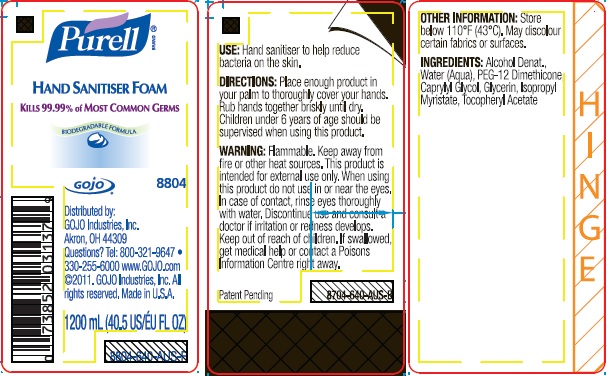 DRUG LABEL: PURELL Antiseptic Hand Foam
NDC: 21749-832 | Form: LIQUID
Manufacturer: GOJO Industries, Inc.
Category: otc | Type: HUMAN OTC DRUG LABEL
Date: 20241231

ACTIVE INGREDIENTS: ALCOHOL 0.7 mL/1 mL
INACTIVE INGREDIENTS: WATER; ISOPROPYL ALCOHOL; PEG-12 DIMETHICONE (300 CST); CAPRYLYL GLYCOL; GLYCERIN; ISOPROPYL MYRISTATE; .ALPHA.-TOCOPHEROL ACETATE

PURELL Antiseptic Hand Foam